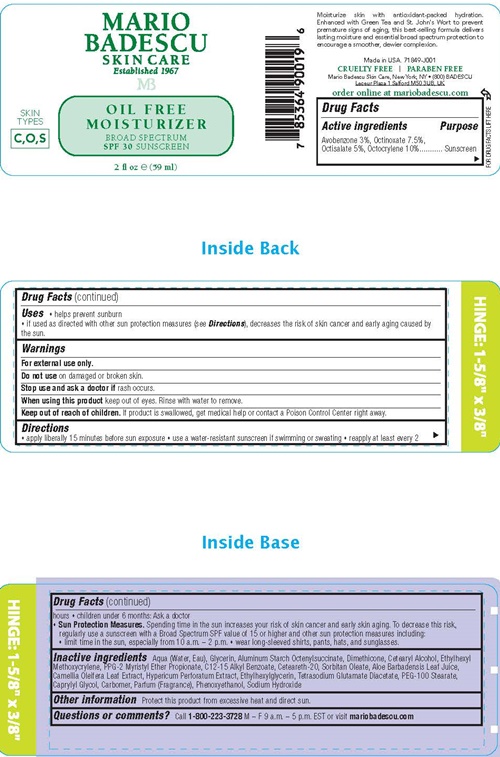 DRUG LABEL: MARIO BADESCU SPF 30
NDC: 54111-134 | Form: LOTION
Manufacturer: Bentley Laboratories LLC
Category: otc | Type: HUMAN OTC DRUG LABEL
Date: 20240910

ACTIVE INGREDIENTS: AVOBENZONE 1.5 g/59 mL; OCTINOXATE 3.75 g/59 mL; OCTISALATE 2.5 g/59 mL; OCTOCRYLENE 5 g/59 mL
INACTIVE INGREDIENTS: WATER; GLYCERIN; ALUMINUM STARCH OCTENYLSUCCINATE; DIMETHICONE; CETOSTEARYL ALCOHOL; ETHYLHEXYL METHOXYCRYLENE; PPG-2 MYRISTYL ETHER PROPIONATE; ALKYL (C12-15) BENZOATE; POLYOXYL 20 CETOSTEARYL ETHER; SORBITAN MONOOLEATE; ALOE VERA LEAF; CAMELLIA OLEIFERA LEAF; HYPERICUM PERFORATUM; ETHYLHEXYLGLYCERIN; TETRASODIUM GLUTAMATE DIACETATE; PEG-100 STEARATE; CAPRYLYL GLYCOL; CARBOXYPOLYMETHYLENE; PHENOXYETHANOL; SODIUM HYDROXIDE

Mario Badescu Oil Free Moisturizer SPF 30

Drug Facts Active ingredients

Avobenzone 3.0%
Octinoxate 7.5%
Octisalate 5.0%
Octocrylene 10.0%

Purpose

Sunscreen

Uses

- helps prevent sunburn
- If used as directed with other sun protection measures (see Directions), decreases the risk of skin cancer and early aging caused by the sun.

Warnings

For external use only.

Do not use on damaged or broken skin.

Stop use and ask a doctor if rash occurs.

When using this product keep out of eyes. Rinse with water to remove

Keep out of reach of children.

If product is swallowed, get medical help or contact a Poison Control Center right away.

Directions

- apply liberally 15 minutes before sun exposure
- use a water-resistant sunscreen if swimming or sweating
- reapply at least every 2 hours
- children under 6 months: Ask a doctor

Sun Protection Measures. Spending time in the sun increases your risk of skin cancer and early skin aging. To decrease this risk, regularly use a sunscreen with a Broad Spectrum SPF value of 15 or higher and other sun protection measures including:

- limit time in the sun, especially from 10 a.m. - 2 p.m.
- wear long-sleeved shirts, pants, hats, and sunglasses.

Inactive ingredients

Aqua (Water, Eau), Glycerin, Aluminum Starch Octenylsuccinate, Dimethicone, Cetearyl Alcohol, Ethylhexyl Methoxycrylene, PPG-2 Myristyl Ether Propionate, C12-15 Alkyl Benzoate, Ceteareth-20, Sorbitan Oleate, Aloe Barbadensis Leaf Juice, Camellia Oleifera Leaf Extract, Hypericum Perforatum Leaf Extract, Ethylhexlglycerin, Tetrasodium Glutamate Diacetate, PEG-100 Stearate, Caprylyl Glycol, Carbomer, Parfum (Fragrance), Phenoxyethanol, Sodium Hydroxide

Other information

Protect this product from excessive heat and direct sun.

Questions or comments?

Call 1-800-223-3728 M - F 9 a.m. - 5 p.m. EST or visit mariobadescu.com

Mario Badescu Oil Free Moisturizer SPF 30 product label

MARIO
BADESCU
SKIN CARE
Established 1967
MB
OIL FREE
MOISTURIZER
BROAD SPECTRUM
SPF 30 SUNSCREEN

SKIN TYPES - C, O, S,

2 fl oz (59 ml)

Moisturize skin with antioxidant-packed hydration. Enhanced with Green Tea and St John's Wort to prevent premature signs of aging, this best- selling formula delivers lasting moisture and essential broad spectrum protection to encourage a smoother dewier complexion,

Made in the USA. 71849-J001

CRUELTY FREE l PARABEN FREE

Mario Badescu Skin Care, New York, NY • (800) BADESCU
Leceur Plaza 1 Salford M50 3UB, UK

order online at mario bedescu.com

res